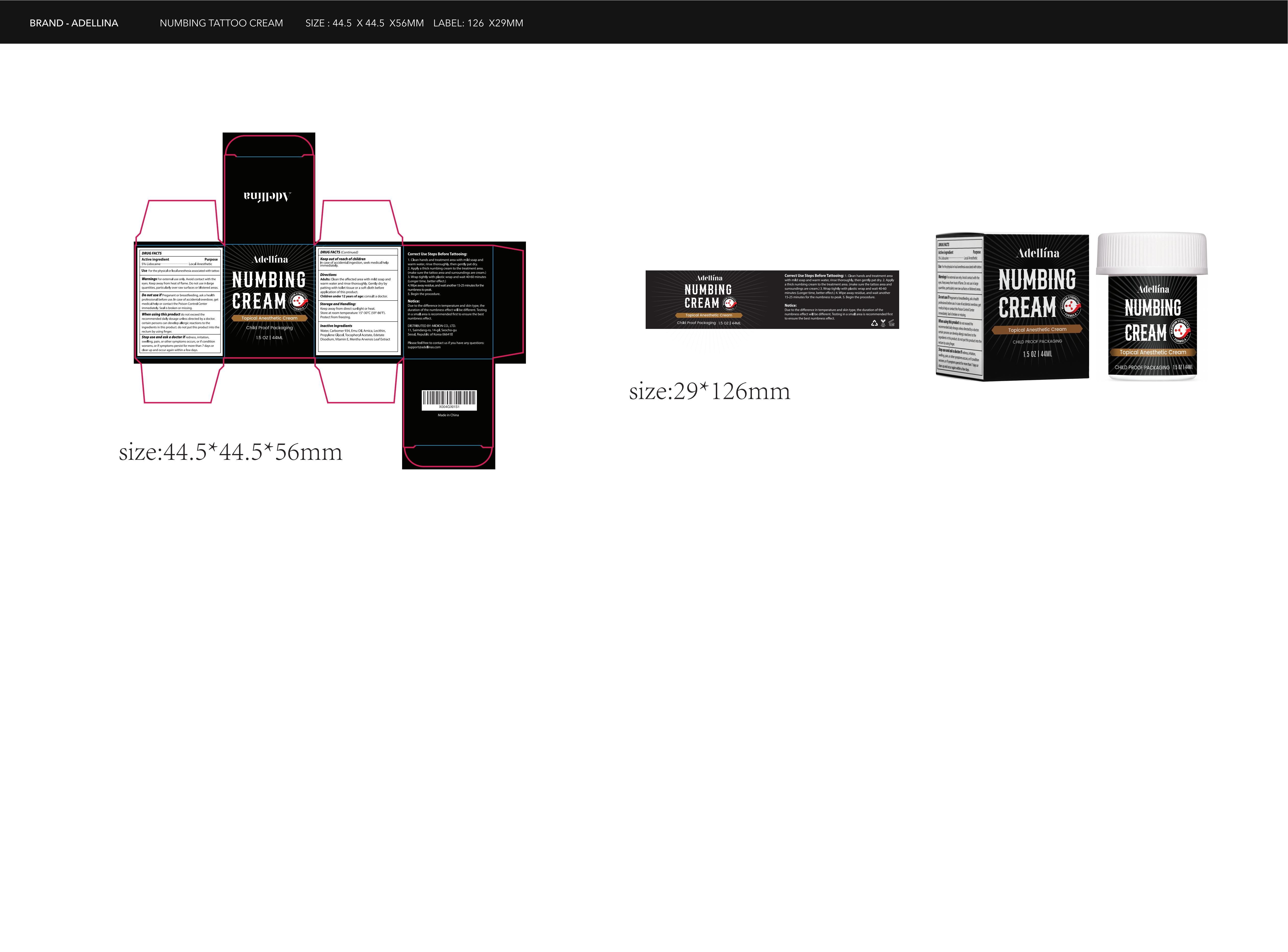 DRUG LABEL: Adellina Numbing Cream
NDC: 60771-0011 | Form: CREAM
Manufacturer: Guangzhou Haishi Biological Technology Co., Ltd.
Category: otc | Type: HUMAN OTC DRUG LABEL
Date: 20250326

ACTIVE INGREDIENTS: LIDOCAINE 5 g/100 mL
INACTIVE INGREDIENTS: GLYCERIN; 1,2-HEXANEDIOL

Adellina Numbing Cream

Active ingredients

Lidocaine 5%

Purpose

Local Anesthetic

Uses

For the physical or local anesthesia associated with tattoo

For external use only.

Avoid contact with the eyes Keep away from heat or flame. Do not use in large quantities, particularly over raw surfaces or blistered areas.

Stop use and ask a doctor if redness, irritation, swelling, pain, or other symptoms occurs,or If condition worsens, or if symptoms persist for more than 7 days or clear up and occur again within a few days.

Do not use this product if Pregnant or breastfeeding, ask a health professional before use. In case of accidental overdose, get medical help or contact the Poison Control Center immediately. Seal is broken or missing.

WHEN USING

Do not exceed the recommended daily dosage unless directed by a doctor. certain persons can develop allergic reactions to ingredients in this product. do not put this product into the rectum by using finger.

Keep out of reach of children

In case of accidental ingestion, seek medical help immediately.

Dosage

Squeeze out an appropriate amount of product and spread evenly on skin.

Inactive ingredients

AQUA 71.3%
PROPYLENE 5%
CARBOMER 0.25%
GLYCERIN 5%
DISODIUM EDTA 0.05%
HYDROXYACETOPHENONE 0.4%
1,2-HEXANEDIOL 5%
MENTHA ARVENSIS LEAF EXTRACT 2%
CHRYSANTHELLUM INDICUM EXTRACT 2%
PORTULACA OLERACEA EXTRACT 2%
PEG-40 HYDROGENATED CASTOR OIL 2%